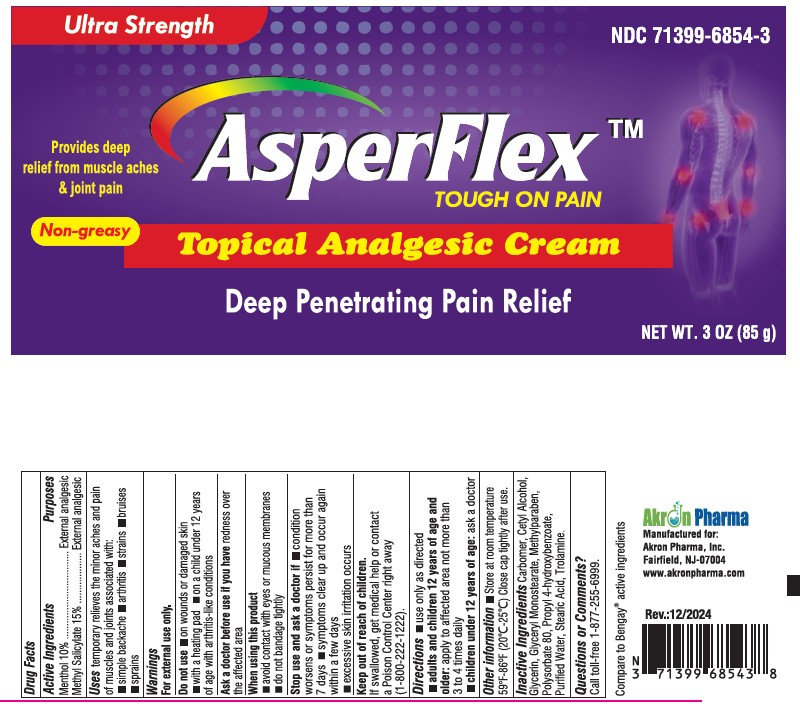 DRUG LABEL: AsperFlex
NDC: 71399-6854 | Form: CREAM
Manufacturer: Akron Pharma Inc.
Category: otc | Type: HUMAN OTC DRUG LABEL
Date: 20260119

ACTIVE INGREDIENTS: MENTHOL 100 mg/1 g; METHYL SALICYLATE 150 mg/1 g
INACTIVE INGREDIENTS: CARBOMER HOMOPOLYMER, UNSPECIFIED TYPE; CETYL ALCOHOL; GLYCERIN; GLYCERYL MONOSTEARATE; METHYLPARABEN; STEARIC ACID; PROPYLPARABEN; POLYSORBATE 80; TROLAMINE; WATER

AsperFlex
Tough on Pain
Non-greasy-Topical Analgesic Cream
Deep Penetrating Pain Relief

Active Ingredient

Menthol 10%

Methyl Salicylate 15 %

Purpose

External analgesic

Uses

temporary relieves the minor aches and pain of muscles and joints associated with:

- simple backache
- arthritis
- strains
- bruises
- sprains

Warnings

For external use only

Do not use

- on wounds or damaged skin
- with a heating pad
- on a child under 12 years of age with arthritis-like conditions

Ask a doctor before use if you have

redness over the affected area

When using this product

- avoid contact with eyes or mucous membranes
- do not bandage tightly

Stop use and ask a doctor if

■condition worsens or symptoms persist for more than 7 days

■ symptoms clear up and occur again within a few days

■ excessive skin irritation occurs

Keep out of reach of children.

If swallowed, get medical help or contact a Poison Control Center right away (1-800-222-1222).

Directions

adults and children 12 years of age and older:

apply to affected area not more than 3 to 4 times daily

children under 12 years of age:consult a doctor

Other Information

store at 20°-25°C (68°-77°F).

Close cap tightly after use.

Inactive ingredients

carbomer homopolymer, cetyl alcohol glycerin,glyceryl monostearate, methylparaben,stearic acid,propyl 4-hydroxybenzoate, polysorbate 80,trolamine, purifed water

Questions or Comments?

Call toll-free 1-877-255-6999.